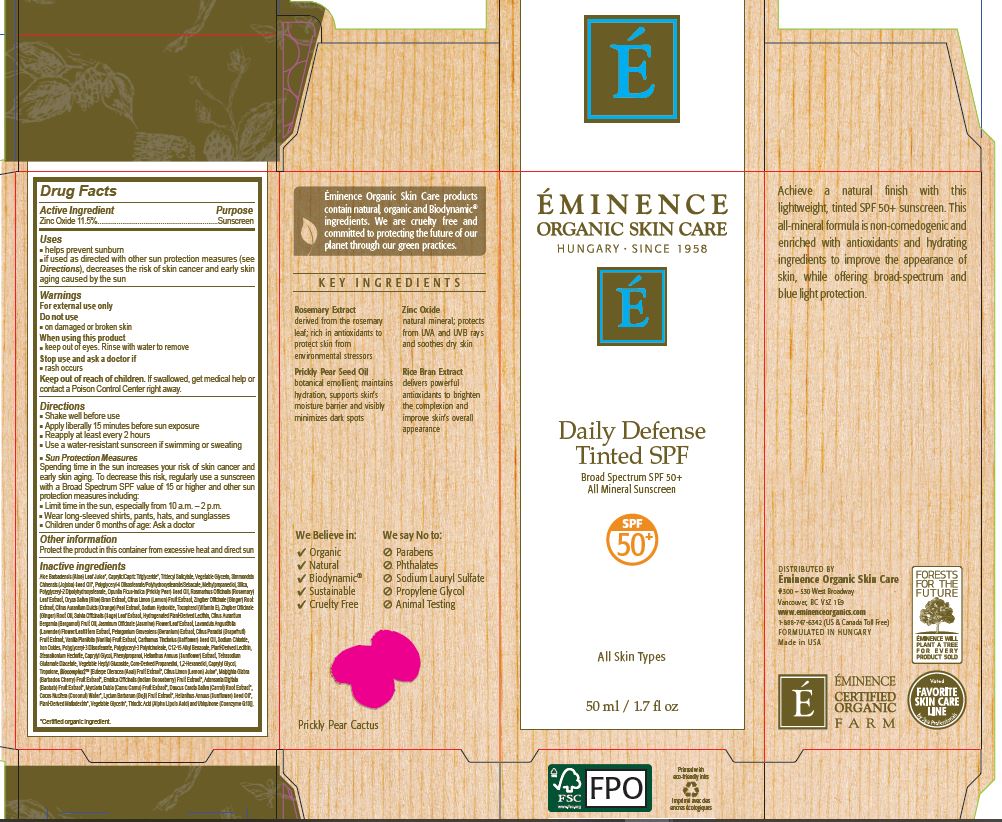 DRUG LABEL: Eminence Daily Defense Tinted SPF
NDC: 15751-3508 | Form: LIQUID
Manufacturer: Eminence Organic Skin Care
Category: otc | Type: HUMAN OTC DRUG LABEL
Date: 20240325

ACTIVE INGREDIENTS: ZINC OXIDE 115 mg/1 mL
INACTIVE INGREDIENTS: HELIANTHUS ANNUUS WHOLE; COCONUT WATER; LYCIUM BARBARUM FRUIT; TETRASODIUM GLUTAMATE DIACETATE; CAPRYLYL GLYCOL; SIMMONDSIA CHINENSIS SEED; ALKYL (C12-15) BENZOATE; PHENYLPROPANOL; SODIUM HYDROXIDE; HYDROGENATED SOYBEAN LECITHIN; MALTODEXTRIN; UBIDECARENONE; GINGER OIL; LAVANDULA ANGUSTIFOLIA FLOWERING TOP; FERRIC OXIDE YELLOW; BERGAMOT OIL; GINGER; LECITHIN, SUNFLOWER; PROPANEDIOL; MALPIGHIA GLABRA FRUIT; MYRCIARIA DUBIA FRUIT; JASMINUM OFFICINALE FLOWER; CITRUS PARADISI FRUIT OIL; ALOE VERA LEAF; SAFFLOWER OIL; POLYGLYCERYL-3 DIISOSTEARATE; HEPTYL GLUCOSIDE; TROPOLONE; EUTERPE OLERACEA WHOLE; PHYLLANTHUS EMBLICA FRUIT; SAGE; VANILLA PLANIFOLIA OIL; CAPRYLIC/CAPRIC/LINOLEIC TRIGLYCERIDE; ROSEMARY; RICE BRAN; CITRUS LIMON FRUIT OIL; CITRUS AURANTIUM FRUIT RIND; TRIDECYL SALICYLATE; GLYCERIN; FERRIC OXIDE RED; STEARALKONIUM HECTORITE; 1,2-HEXANEDIOL; ADANSONIA DIGITATA FRUIT; POLYGLYCERYL-4 DIISOSTEARATE/POLYHYDROXYSTEARATE/SEBACATE; SILICON DIOXIDE; TOCOPHEROL; PELARGONIUM GRAVEOLENS FLOWER OIL; SODIUM CHLORIDE; THIOCTIC ACID; POLYGLYCERYL-3 RICINOLEATE; METHYLPROPANEDIOL; OPUNTIA FICUS-INDICA SEED OIL; DAUCUS CAROTA ROOT OIL; POLYGLYCERYL-2 DIPOLYHYDROXYSTEARATE; LEMON JUICE; SUNFLOWER SEED

Daily Defense Tinted SPF

Daily Defense Tinted SPF

Drug Facts

Active Ingredient Purpose

Zinc Oxide 11.5%……………………...Sunscreen

Uses

helps prevent sunburn
if used as directed with other sun protection measures (see Directions), decreases the risk of skin cancer and early skin aging caused by the sun

Warnings

For external use only

Do not use

on damaged or broken skin

When using this product

keep out of eyes. Rinse with water to remove

Stop use and ask doctor if

rash occurs

Keep out of reach of children. If swallowed, get medical help or contact a Poison Control Center right away.

Directions

Shake well before use
Apply liberally 15 minutes before sun exposure
Reapply at least every 2 hours
Use a water-resistant sunscreen if swimming or sweating.

Sun Protection Measures

Spending time in the sun increases your risk of skin cancer and early skin aging. To decrease this risk, regularly use a sunscreen with a Broad Spectrum SPF value of 15 or higher and other sun protection measures including:

Limit time in the sun, especially from 10 a.m. – 2 p.m.
Wear long-sleeved shirts, pants, hats, and sunglasses.
Children under 6 months of age: Ask a doctor.

Other information

Protect the product in this container from excessive heat and direct sun.

Inactive ingredients

Aloe Barbadensis (Aloe) Leaf Juice*, Caprylic/Capric Triglyceride*, Tridecyl Salicylate, Vegetable Glycerin, Simmondsia Chinensis (Jojoba) Seed Oil*, Polyglyceryl-4 Diisostearate/Polyhydroxystearate/Sebacate, Methylpropanediol, Silica, Polyglyceryl-2 Dipolyhydroxystearate, Opuntia Ficus-Indica (Prickly Pear) Seed Oil, Rosmarinus Officinalis (Rosemary) Leaf Extract, Oryza Sativa (Rice) Bran Extract, Citrus Limon (Lemon) Fruit Extract, Zingiber Officinale (Ginger) Root Extract, Citrus Aurantium Dulcis (Orange) Peel Extract, Sodium Hydroxide, Tocopherol (Vitamin E), Zingiber Officinale (Ginger) Root Oil, Salvia Officinalis (Sage) Leaf Extract, Hydrogenated Plant-Derived Lecithin, Citrus Aurantium Bergamia (Bergamot) Fruit Oil, Jasminum Officinale (Jasmine) Flower/Leaf Extract, Lavandula Angustifolia (Lavender) Flower/Leaf/Stem Extract, Pelargonium Graveolens (Geranium) Extract, Citrus Paradisi (Grapefruit) Fruit Extract, Vanilla Planifolia (Vanilla) Fruit Extract, Carthamus Tinctorius (Safflower) Seed Oil, Sodium Chloride, Iron Oxides, Polyglyceryl-3 Diisostearate, Polyglyceryl-3 Polyricinoleate, C12-15 Alkyl Benzoate, Plant-Derived Lecithin, Stearalkonium Hectorite, Caprylyl Glycol, Phenylpropanol, Helianthus Annuus (Sunflower) Extract, Tetrasodium Glutamate Diacetate, Vegetable Heptyl Glucoside, Corn-Derived Propanediol, 1,2-Hexanediol, Caprylyl Glycol, Tropolone, Biocomplex2™ [Euterpe Oleracea (Acai) Fruit Extract*, Citrus Limon (Lemon) Juice*, Malpighia Glabra (Barbados Cherry) Fruit Extract*, Emblica Officinalis (Indian Gooseberry) Fruit Extract*, Adansonia Digitata (Baobab) Fruit Extract*, Myrciaria Dubia (Camu Camu) Fruit Extract*, Daucus Carota Sativa (Carrot) Root Extract*, Cocos Nucifera (Coconut) Water*, Lycium Barbarum (Goji) Fruit Extract*, Helianthus Annuus (Sunflower) Seed Oil*, Plant-Derived Maltodextrin*, Vegetable Glycerin*, Thioctic Acid (Alpha Lipoic Acid) and Ubiquinone (Coenzyme Q10)].

DISTRIBUTED BY

Éminence Organic Skin Care

#300 - 530 West Broadway, Vancouver BC V5Z 1E9

www.eminenceorganics.com

1-888-747-6342 (US & Canada Toll Free)

FORMULATED IN HUNGARY / Made in USA

Refer to Daily Defense Tinted SPF US 1.7oz

Directions

Shake well before use
Apply liberally 15 minutes before sun exposure
Reapply at least every 2 hours
Use a water-resistant sunscreen if swimming or sweating.

Sun Protection Measures

Spending time in the sun increases your risk of skin cancer and early skin aging. To decrease this risk, regularly use a sunscreen with a Broad Spectrum SPF value of 15 or higher and other sun protection measures including:

Limit time in the sun, especially from 10 a.m. – 2 p.m.
Wear long-sleeved shirts, pants, hats, and sunglasses.
Children under 6 months of age: Ask a doctor.

Warnings

For external use only

Do not use on damaged or broken skin

When using this product keep out of eyes. Rinse with water to remove

Stop use and ask doctor if rash occurs

Inactive Ingredients

Aloe Barbadensis (Aloe) Leaf Juice*, Caprylic/Capric Triglyceride*, Tridecyl Salicylate, Vegetable Glycerin, Simmondsia Chinensis (Jojoba) Seed Oil*, Polyglyceryl-4 Diisostearate/Polyhydroxystearate/Sebacate, Methylpropanediol, Silica, Polyglyceryl-2 Dipolyhydroxystearate, Opuntia Ficus-Indica (Prickly Pear) Seed Oil, Rosmarinus Officinalis (Rosemary) Leaf Extract, Oryza Sativa (Rice) Bran Extract, Citrus Limon (Lemon) Fruit Extract, Zingiber Officinale (Ginger) Root Extract, Citrus Aurantium Dulcis (Orange) Peel Extract, Sodium Hydroxide, Tocopherol (Vitamin E), Zingiber Officinale (Ginger) Root Oil, Salvia Officinalis (Sage) Leaf Extract, Hydrogenated Plant-Derived Lecithin, Citrus Aurantium Bergamia (Bergamot) Fruit Oil, Jasminum Officinale (Jasmine) Flower/Leaf Extract, Lavandula Angustifolia (Lavender) Flower/Leaf/Stem Extract, Pelargonium Graveolens (Geranium) Extract, Citrus Paradisi (Grapefruit) Fruit Extract, Vanilla Planifolia (Vanilla) Fruit Extract, Carthamus Tinctorius (Safflower) Seed Oil, Sodium Chloride, Iron Oxides, Polyglyceryl-3 Diisostearate, Polyglyceryl-3 Polyricinoleate, C12-15 Alkyl Benzoate, Plant-Derived Lecithin, Stearalkonium Hectorite, Caprylyl Glycol, Phenylpropanol, Helianthus Annuus (Sunflower) Extract, Tetrasodium Glutamate Diacetate, Vegetable Heptyl Glucoside, Corn-Derived Propanediol, 1,2-Hexanediol, Caprylyl Glycol, Tropolone, Biocomplex2™ [Euterpe Oleracea (Acai) Fruit Extract*, Citrus Limon (Lemon) Juice*, Malpighia Glabra (Barbados Cherry) Fruit Extract*, Emblica Officinalis (Indian Gooseberry) Fruit Extract*, Adansonia Digitata (Baobab) Fruit Extract*, Myrciaria Dubia (Camu Camu) Fruit Extract*, Daucus Carota Sativa (Carrot) Root Extract*, Cocos Nucifera (Coconut) Water*, Lycium Barbarum (Goji) Fruit Extract*, Helianthus Annuus (Sunflower) Seed Oil*, Plant-Derived Maltodextrin*, Vegetable Glycerin*, Thioctic Acid (Alpha Lipoic Acid) and Ubiquinone (Coenzyme Q10)].

Uses

helps prevent sunburn
if used as directed with other sun protection measures (see Directions), decreases the risk of skin cancer and early skin aging caused by the sun

Keep out of reach of children. If swallowed, get medical help or contact a Poison Control Center right away.

Active Ingredient Purpose

Zinc Oxide 11.5%……………………...Sunscreen